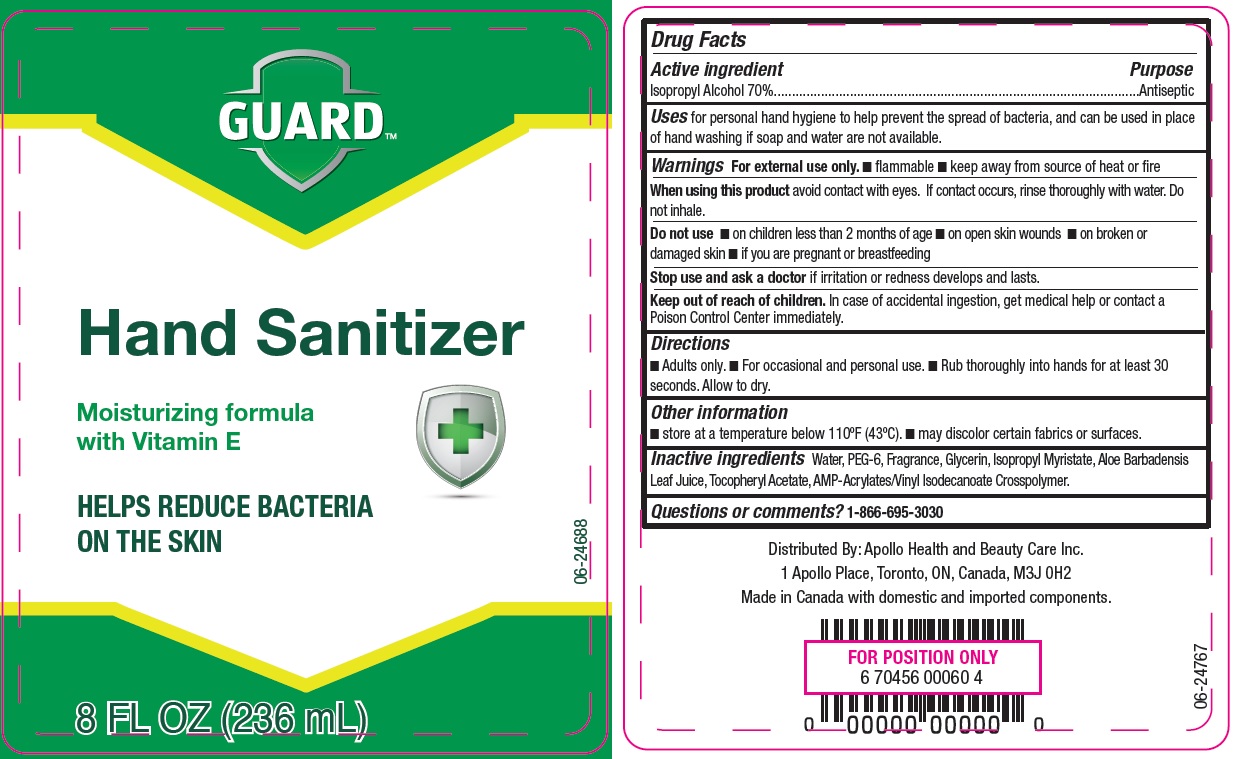 DRUG LABEL: Guard Hand Sanitizer
NDC: 63148-519 | Form: GEL
Manufacturer: Apollo Health and Beauty Care Inc.
Category: otc | Type: HUMAN OTC DRUG LABEL
Date: 20250105

ACTIVE INGREDIENTS: ISOPROPYL ALCOHOL 700 mg/1 mL
INACTIVE INGREDIENTS: WATER; CETEARETH-6; GLYCERIN; ALOE VERA LEAF; .ALPHA.-TOCOPHEROL ACETATE, DL-; ISOPROPYL MYRISTATE

NDC- 63148-519

Active ingredient

Isopropyl Alcohol 70%

Purpose

Antiseptic

Uses

for personal hand hygiene to help prevent the spread of bacterial, and can be used in place of hand washing if soap and water are not available.

For external use only

- flammable
- keep away from source of heat or fire

When using this product

avoid contact with eyes. If contact occurs, rinse thoroughly with water. Do not inhale.

Do not use

- on children less than 2 months of age
- on open skin wounds
- on broken or damaged skin
- if you are pregnant or breastfeeding

Stop use and ask a doctor if

irritation or redness develops and lasts.

Keep out of reach of children.

In case of accidental ingestion, get medical help or contact a Poison Control Center immediately.

Directions

- Adults only
- For occasional and personal use
- Rub thoroughly into hands for at least 30 seconds. Allow to dry.

Other information

- store at a temperature below 110°F (43°C)
- may discolor certain fabrics or surfaces

Inactive ingredients

Water, PEG-6, Fragrance, Glycerin, Isopropyl Myristate, Aloe Barbadensis Leaf Juice, Tocopheryl Acetate, AMP-Acrylates/Vinyl Isodecanoate Crosspolymer.

Questions or comments?

1-866-695-3030